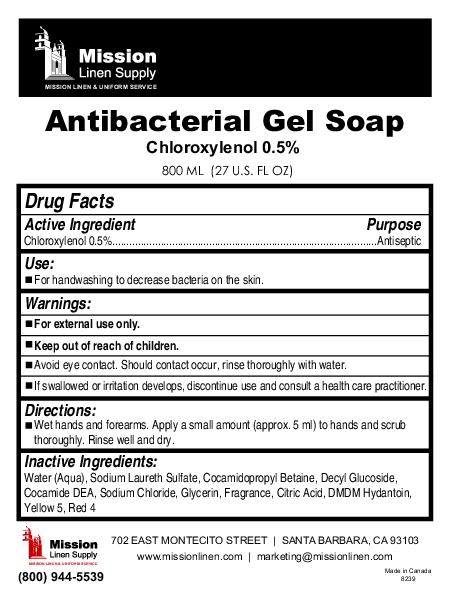 DRUG LABEL: Antibacterial Soap
NDC: 51053-502 | Form: GEL
Manufacturer: Sanihealth Products Corporation
Category: otc | Type: HUMAN OTC DRUG LABEL
Date: 20100510

ACTIVE INGREDIENTS: chloroxylenol 4 mL/800 mL

Antibacterial Soap

Directions:

Wet hands and forearms. Apply a small amount (approx. 5 ml) to hands and scrub thoroughly. Rinse well and dry.

Inactive Ingredients:

Water (aqua) sodium laureth sulfate, cocamidopropyl betaine, decyl glucoside, Cocamide DEA, sodium chloride, glycerin, fragrance, citric acid, DMDM hydantoin, Yellow 5, Red 4

Use:

For handwashing to decrease bacteria on the skin.

Active Ingredient Purpose

Chloroxylenol 0.5% Antiseptic

Warnings:

For external use only.

Keep out of reach of children.

Avoid eye contact. Should contact occur, rinse thoroughly with water.

If swallowed or irritation develops, discontinue use and consult a health care practitioner.

PACKAGE LABEL

Antibacterial gel Soap

Chloroxylenol 0.5%

800 ml (27 US fl oz)